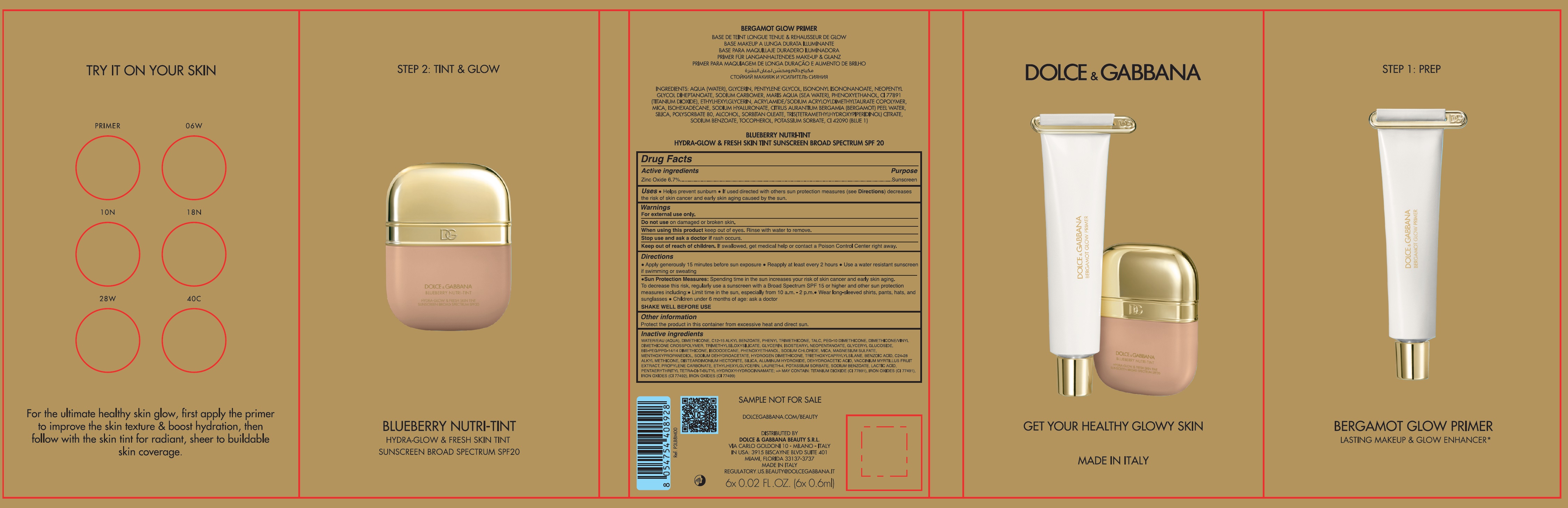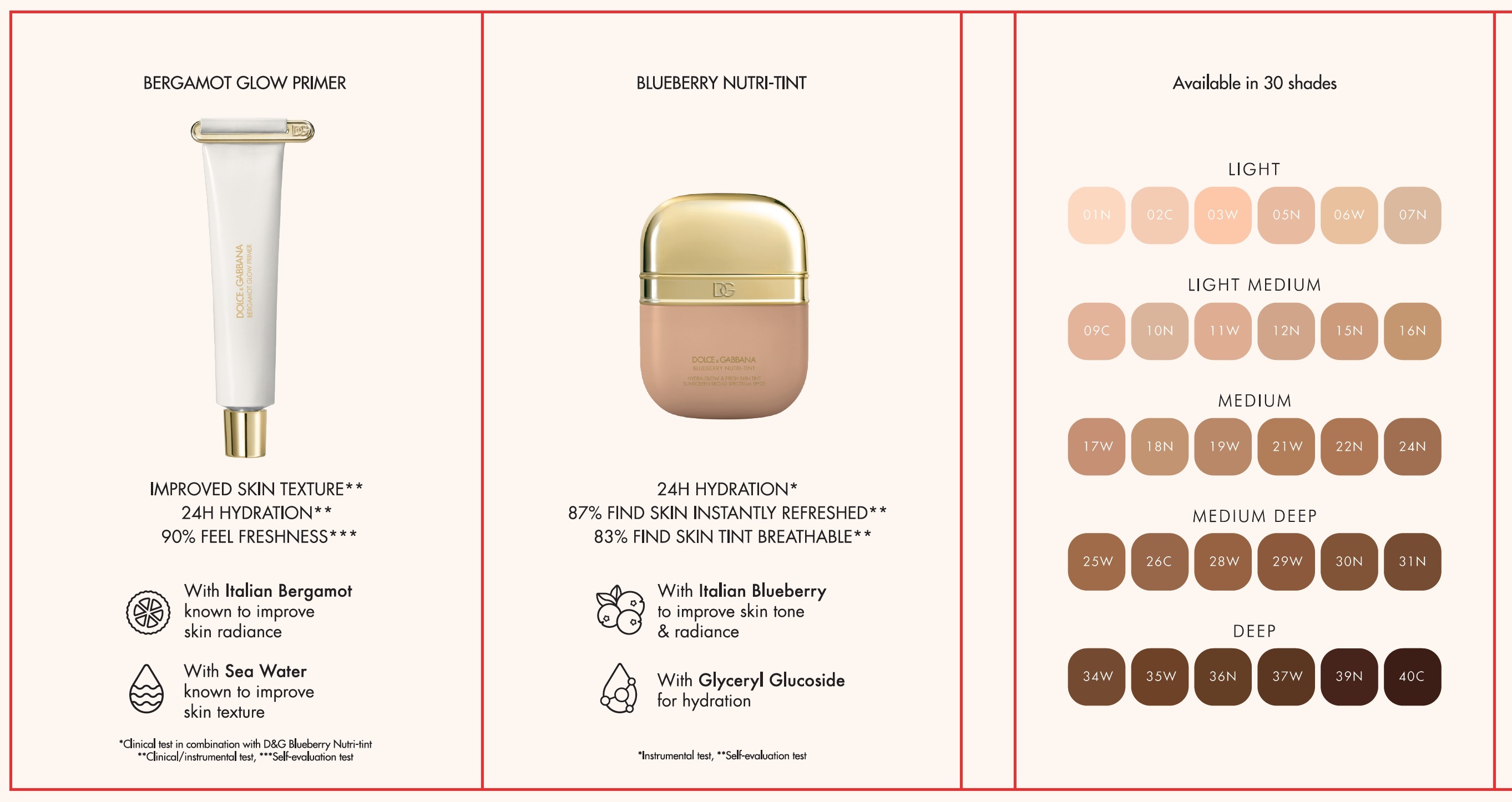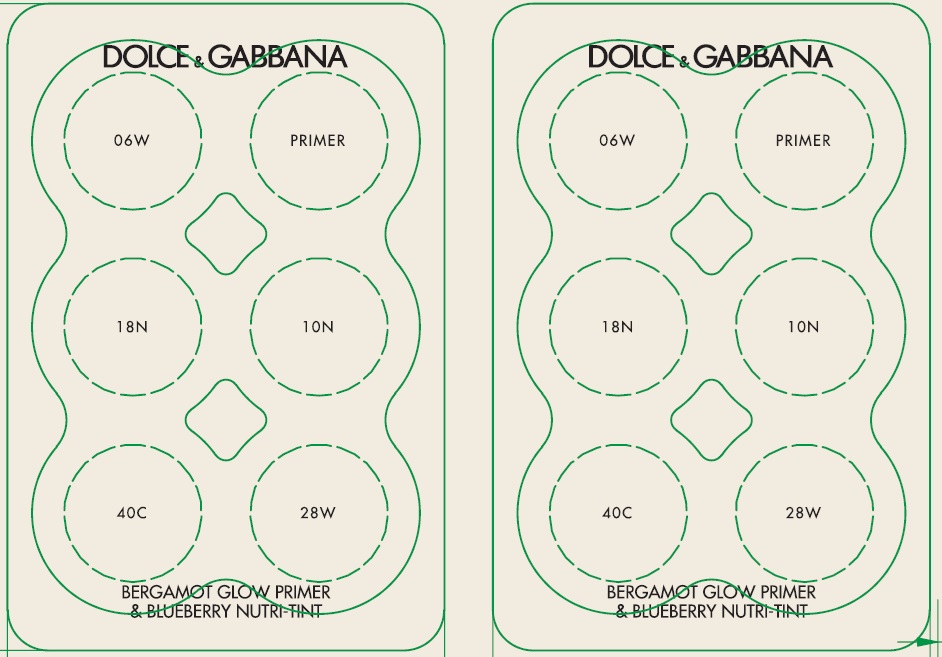 DRUG LABEL: Dolce and Gabbana Get Your Healthy Glowy Skin Bergamot Glow Primer Blueberry Nutri Tint
NDC: 84003-077 | Form: KIT | Route: TOPICAL
Manufacturer: Dolce & Gabbana Beauty S.R.L
Category: otc | Type: HUMAN OTC DRUG LABEL
Date: 20250912

ACTIVE INGREDIENTS: ZINC OXIDE 67 mg/1 mL; ZINC OXIDE 67 mg/1 mL; ZINC OXIDE 67 mg/1 mL; ZINC OXIDE 67 mg/1 mL; ZINC OXIDE 67 mg/1 mL
INACTIVE INGREDIENTS: WATER; DIMETHICONE; ALKYL (C12-15) BENZOATE; PHENYL TRIMETHICONE; TALC; GLYCERIN; ISOSTEARYL NEOPENTANOATE; GLYCERYL GLUCOSIDE; BIS-PEG/PPG-14/14 DIMETHICONE; ISODODECANE; PHENOXYETHANOL; SODIUM CHLORIDE; MICA; MAGNESIUM SULFATE, UNSPECIFIED FORM; 3-((L-MENTHYL)OXY)PROPANE-1,2-DIOL; SODIUM DEHYDROACETATE; TRIETHOXYCAPRYLYLSILANE; BENZOIC ACID; DISTEARDIMONIUM HECTORITE; SILICON DIOXIDE; ALUMINUM HYDROXIDE; DEHYDROACETIC ACID; BILBERRY; PROPYLENE CARBONATE; ETHYLHEXYLGLYCERIN; LAURETH-4; POTASSIUM SORBATE; SODIUM BENZOATE; LACTIC ACID; PENTAERYTHRITOL TETRAKIS(3-(3,5-DI-TERT-BUTYL-4-HYDROXYPHENYL)PROPIONATE); WATER; DIMETHICONE; ALKYL (C12-15) BENZOATE; PHENYL TRIMETHICONE; TALC; GLYCERIN; ISOSTEARYL NEOPENTANOATE; GLYCERYL GLUCOSIDE; BIS-PEG/PPG-14/14 DIMETHICONE; ISODODECANE; PHENOXYETHANOL; SODIUM CHLORIDE; MICA; MAGNESIUM SULFATE, UNSPECIFIED FORM; 3-((L-MENTHYL)OXY)PROPANE-1,2-DIOL; SODIUM DEHYDROACETATE; TRIETHOXYCAPRYLYLSILANE; BENZOIC ACID; DISTEARDIMONIUM HECTORITE; SILICON DIOXIDE; ALUMINUM HYDROXIDE; DEHYDROACETIC ACID; BILBERRY; PROPYLENE CARBONATE; ETHYLHEXYLGLYCERIN; LAURETH-4; POTASSIUM SORBATE; SODIUM BENZOATE; LACTIC ACID; PENTAERYTHRITOL TETRAKIS(3-(3,5-DI-TERT-BUTYL-4-HYDROXYPHENYL)PROPIONATE); WATER; DIMETHICONE; ALKYL (C12-15) BENZOATE; PHENYL TRIMETHICONE; TALC; GLYCERIN; ISOSTEARYL NEOPENTANOATE; GLYCERYL GLUCOSIDE; BIS-PEG/PPG-14/14 DIMETHICONE; ISODODECANE; PHENOXYETHANOL; SODIUM CHLORIDE; MICA; MAGNESIUM SULFATE, UNSPECIFIED FORM; 3-((L-MENTHYL)OXY)PROPANE-1,2-DIOL; SODIUM DEHYDROACETATE; TRIETHOXYCAPRYLYLSILANE; BENZOIC ACID; DISTEARDIMONIUM HECTORITE; SILICON DIOXIDE; ALUMINUM HYDROXIDE; DEHYDROACETIC ACID; BILBERRY; PROPYLENE CARBONATE; ETHYLHEXYLGLYCERIN; LAURETH-4; POTASSIUM SORBATE; SODIUM BENZOATE; LACTIC ACID; PENTAERYTHRITOL TETRAKIS(3-(3,5-DI-TERT-BUTYL-4-HYDROXYPHENYL)PROPIONATE); WATER; DIMETHICONE; ALKYL (C12-15) BENZOATE; PHENYL TRIMETHICONE; TALC; GLYCERIN; ISOSTEARYL NEOPENTANOATE; GLYCERYL GLUCOSIDE; BIS-PEG/PPG-14/14 DIMETHICONE; ISODODECANE; PHENOXYETHANOL; SODIUM CHLORIDE; MICA; MAGNESIUM SULFATE, UNSPECIFIED FORM; 3-((L-MENTHYL)OXY)PROPANE-1,2-DIOL; SODIUM DEHYDROACETATE; TRIETHOXYCAPRYLYLSILANE; BENZOIC ACID; DISTEARDIMONIUM HECTORITE; SILICON DIOXIDE; ALUMINUM HYDROXIDE; DEHYDROACETIC ACID; BILBERRY; PROPYLENE CARBONATE; ETHYLHEXYLGLYCERIN; LAURETH-4; POTASSIUM SORBATE; SODIUM BENZOATE; LACTIC ACID; PENTAERYTHRITOL TETRAKIS(3-(3,5-DI-TERT-BUTYL-4-HYDROXYPHENYL)PROPIONATE); WATER; DIMETHICONE; ALKYL (C12-15) BENZOATE; PHENYL TRIMETHICONE; TALC; GLYCERIN; ISOSTEARYL NEOPENTANOATE; GLYCERYL GLUCOSIDE; BIS-PEG/PPG-14/14 DIMETHICONE; ISODODECANE; PHENOXYETHANOL; SODIUM CHLORIDE; MICA; MAGNESIUM SULFATE, UNSPECIFIED FORM; 3-((L-MENTHYL)OXY)PROPANE-1,2-DIOL; SODIUM DEHYDROACETATE; TRIETHOXYCAPRYLYLSILANE; BENZOIC ACID; DISTEARDIMONIUM HECTORITE; SILICON DIOXIDE; ALUMINUM HYDROXIDE; DEHYDROACETIC ACID; BILBERRY; PROPYLENE CARBONATE; ETHYLHEXYLGLYCERIN; LAURETH-4; POTASSIUM SORBATE; SODIUM BENZOATE; LACTIC ACID; PENTAERYTHRITOL TETRAKIS(3-(3,5-DI-TERT-BUTYL-4-HYDROXYPHENYL)PROPIONATE)

Dolce & Gabbana Get Your Healthy Glowy Skin Bergamot Glow Primer Blueberry Nutri-Tint

Active ingredients

Zinc Oxide 6.7%

Purpose

Sunscreen

Uses

- Helps prevent sunburn
- If uses directed with others sun protection measures (see Directions) decreases the risk of skin cancer and early skin aging caused by the sun.

Warnings

For external use only.

Do not use

on damaged or broken skin.

When using this product

keep out of eyes. Rinse with water to remove.

Stop use and ask a doctor if

rash occurs.

Keep out of reach of children.

If swallowed, get medical help or contact a Poison Control Center right away

Directions

- Apply generously 15 minutes before sun exposure
- Reapply at least every 2 hours
- Use a water resistant sunscreen if swimming or sweating
- Sun Protection Measures:Spending time in the sun increases your risk of skin cancer and early skin aging. To decrease this risk, regularly use a sunscreen with a Broad Spectrum SPF 15 or higher and other sun protection measures including:
- Limit time in the sun, especially from 10 a.m. - 2 p.m.
- Wear long-sleeved shirts, pants, hats, and sunglasses
- Children under 6 months of age: ask a doctor

SHAKE WELL BEFORE USE

Other information

Protect the product in this container from excessive heat and direct sun.

Inactive ingredients

WATER/EAU (AQUA), DIMETHICONE, C12-15 ALKYL BENZOATE, PHENYL TRIMETHICONE, TALC, PEG-10 DIMETHICONE, DIMETHICONE/VINYL DIMETHICONE CROSSPOLYMER, TRIMETHYLSILOXYSILICATE, GLYCERIN, ISOSTEARYL NEOPENTANOATE, GLYCERYL GLUCOSIDE, BIS-PEG/PPG 14/14 DIMETHICONE, ISODODECANE, PHENOXYETHANOL, SODIUM CHLORIDE, MICA, MAGNESIUM SULFATE, MENTHOXYPROPANEDIOL, SODIUM DEHYDROACETATE, HYDROGEN DIMETHICONE, TRIETHOXYCAPRYLYLSILANE, BENZOIC ACID, C24-28 ALKYL METHICONE, DISTEARDIMONIUM HECTORITE, SILICA, ALUMINUM HYDROXIDE, DEHYDROACETIC ACID, VACCINIUM MYRTILLUS FRUIT EXTRACT, PROPYLENE CARBONATE, ETHYLHEXYLGLYCERIN, LAURETH-4, POTASSIUM SORBATE, SODIUM BENZOATE, LACTIC ACID, PENTAERYTHRITYL TETRA-DI-T-BUTYL HYDROXYHYDROCINNAMATE: +/- MAY CONTAIN: TITANIUM DIOXIDE (CI 77891), IRON OXIDES (CI 77491), IRON OXIDES (CI 77492), IRON OXIDES (CI 77499)

Active ingredients

Zinc Oxide 6.7%

Purpose

Sunscreen

Uses

- Helps prevent sunburn
- If uses directed with others sun protection measures (see Directions) decreases the risk of skin cancer and early skin aging caused by the sun.

Warnings

For external use only.

Do not use

on damaged or broken skin.

When using this product

keep out of eyes. Rinse with water to remove.

Stop use and ask a doctor if

rash occurs.

Keep out of reach of children.

If swallowed, get medical help or contact a Poison Control Center right away

Directions

- Apply generously 15 minutes before sun exposure
- Reapply at least every 2 hours
- Use a water resistant sunscreen if swimming or sweating
- Sun Protection Measures:Spending time in the sun increases your risk of skin cancer and early skin aging. To decrease this risk, regularly use a sunscreen with a Broad Spectrum SPF 15 or higher and other sun protection measures including:
- Limit time in the sun, especially from 10 a.m. - 2 p.m.
- Wear long-sleeved shirts, pants, hats, and sunglasses
- Children under 6 months of age: ask a doctor

SHAKE WELL BEFORE USE

Other information

Protect the product in this container from excessive heat and direct sun.

Inactive ingredients

WATER/EAU (AQUA), DIMETHICONE, C12-15 ALKYL BENZOATE, PHENYL TRIMETHICONE, TALC, PEG-10 DIMETHICONE, DIMETHICONE/VINYL DIMETHICONE CROSSPOLYMER, TRIMETHYLSILOXYSILICATE, GLYCERIN, ISOSTEARYL NEOPENTANOATE, GLYCERYL GLUCOSIDE, BIS-PEG/PPG 14/14 DIMETHICONE, ISODODECANE, PHENOXYETHANOL, SODIUM CHLORIDE, MICA, MAGNESIUM SULFATE, MENTHOXYPROPANEDIOL, SODIUM DEHYDROACETATE, HYDROGEN DIMETHICONE, TRIETHOXYCAPRYLYLSILANE, BENZOIC ACID, C24-28 ALKYL METHICONE, DISTEARDIMONIUM HECTORITE, SILICA, ALUMINUM HYDROXIDE, DEHYDROACETIC ACID, VACCINIUM MYRTILLUS FRUIT EXTRACT, PROPYLENE CARBONATE, ETHYLHEXYLGLYCERIN, LAURETH-4, POTASSIUM SORBATE, SODIUM BENZOATE, LACTIC ACID, PENTAERYTHRITYL TETRA-DI-T-BUTYL HYDROXYHYDROCINNAMATE: +/- MAY CONTAIN: TITANIUM DIOXIDE (CI 77891), IRON OXIDES (CI 77491), IRON OXIDES (CI 77492), IRON OXIDES (CI 77499)

Active ingredients

Zinc Oxide 6.7%

Purpose

Sunscreen

Uses

- Helps prevent sunburn
- If uses directed with others sun protection measures (see Directions) decreases the risk of skin cancer and early skin aging caused by the sun.

Warnings

For external use only.

Do not use

on damaged or broken skin.

When using this product

keep out of eyes. Rinse with water to remove.

Stop use and ask a doctor if

rash occurs.

Keep out of reach of children.

If swallowed, get medical help or contact a Poison Control Center right away.

Directions

- Apply generously 15 minutes before sun exposure
- Reapply at least every 2 hours
- Use a water resistant sunscreen if swimming or sweating
- Sun Protection Measures:Spending time in the sun increases your risk of skin cancer and early skin aging. To decrease this risk, regularly use a sunscreen with a Broad Spectrum SPF 15 or higher and other sun protection measures including:
- Limit time in the sun, especially from 10 a.m. - 2 p.m.
- Wear long-sleeved shirts, pants, hats, and sunglasses
- Children under 6 months of age: ask a doctor

SHAKE WELL BEFORE USE

Other information

Protect the product in this container from excessive heat and direct sun.

Inactive ingredients

WATER/EAU (AQUA), DIMETHICONE, C12-15 ALKYL BENZOATE, PHENYL TRIMETHICONE, TALC, PEG-10 DIMETHICONE, DIMETHICONE/VINYL DIMETHICONE CROSSPOLYMER, TRIMETHYLSILOXYSILICATE, GLYCERIN, ISOSTEARYL NEOPENTANOATE, GLYCERYL GLUCOSIDE, BIS-PEG/PPG-14/14 DIMETHICONE, ISODODECANE, PHENOXYETHANOL, SODIUM CHLORIDE, MICA, MAGNESIUM SULFATE, MENTHOXYPROPANEDIOL, SODIUM DEHYDROACETATE, HYDROGEN DIMETHICONE, TRIETHOXYCAPRYLYLSILANE, BENZOIC ACID, C24-28 ALKYL METHICONE, DISTEARDIMONIUM HECTORITE, SILICA, ALUMINUM HYDROXIDE, DEHYDROACETIC ACID, VACCINIUM MYRTILLUS FRUIT EXTRACT, PROPYLENE CARBONATE, ETHYLHEXYLGLYCERIN, LAURETH-4, POTASSIUM SORBATE, SODIUM BENZOATE, LACTIC ACID, PENTAERYTHRITYL TETRA-DI-T-BUTYL HYDROXYHYDROCINNAMATE: +/- MAY CONTAIN: TITANIUM DIOXIDE (CI 77891), IRON OXIDES (CI 77491), IRON OXIDES (CI 77492), IRON OXIDES (CI 77499)

Active ingredients

Zinc Oxide 6.7%

Purpose

Sunscreen

Uses

- Helps prevent sunburn
- If uses directed with others sun protection measures (see Directions) decreases the risk of skin cancer and early skin aging caused by the sun.

Warnings

For external use only.

Do not use

on damaged or broken

When using this product

keep out of eyes. Rinse with water to remove.

Stop use and ask a doctor if

rash occurs.

Keep out of reach of children.

If swallowed, get medical help or contact a Poison Control Center right away.

Directions

- Apply generously 15 minutes before sun exposure
- Reapply at least every 2 hours
- Use a water resistant sunscreen if swimming or sweating
- Sun Protection Measures:Spending time in the sun increases your risk of skin cancer and early skin aging. To decrease this risk, regularly use a sunscreen with a Broad Spectrum SPF 15 or higher and other sun protection measures including:
- Limit time in the sun, especially from 10 a.m. - 2 p.m.
- Wear long-sleeved shirts, pants, hats, and sunglasses
- Children under 6 months of age: ask a doctor

SHAKE WELL BEFORE USE

Other information

Protect the product in this container from excessive heat and direct sun.

Inactive ingredients

WATER/EAU (AQUA), DIMETHICONE, C12-15 ALKYL BENZOATE, PHENYL TRIMETHICONE, TALC, PEG-10 DIMETHICONE, DIMETHICONE/VINYL DIMETHICONE CROSSPOLYMER, TRIMETHYLSILOXYSILICATE, GLYCERIN, ISOSTEARYL NEOPENTANOATE, GLYCERYL GLUCOSIDE, BIS-PEG/PPG-14/14 DIMETHICONE, ISODODECANE, PHENOXYETHANOL, SODIUM CHLORIDE, MICA, MAGNESIUM SULFATE, MENTHOXYPROPANEDIOL, SODIUM DEHYDROACETATE, HYDROGEN DIMETHICONE, TRIETHOXYCAPRYLYLSILANE, BENZOIC ACID, C24-28 ALKYL METHICONE, DISTEARDIMONIUM HECTORITE, SILICA, ALUMINUM HYDROXIDE, DEHYDROACETIC ACID, VACCINIUM MYRTILLUS FRUIT EXTRACT, PROPYLENE CARBONATE, ETHYLHEXYLGLYCERIN, LAURETH-4, POTASSIUM SORBATE, SODIUM BENZOATE, LACTIC ACID, PENTAERYTHRITYL TETRA-DI-T-BUTYL HYDROXYHYDROCINNAMATE: +/- MAY CONTAIN: TITANIUM DIOXIDE (CI 77891), IRON OXIDES (CI 77491), IRON OXIDES (CI 77492), IRON OXIDES (CI 77499)

Active ingredients

Zinc Oxide 6.7%

Purpose

Sunscreen

Uses

- Helps prevent sunburn
- If uses directed with others sun protection measures (see Directions) decreases the risk of skin cancer and early skin aging caused by the sun.

Warnings

For external use only.

Do not use

on damaged or broken skin.

When using this product

keep out of eyes. Rinse with water to remove.

Stop use and ask a doctor if

rash occurs.

Keep out of reach of children.

If swallowed, get medical help or contact a Poison Control Center right away.

Directions

- Apply generously 15 minutes before sun exposure
- Reapply at least every 2 hours
- Use a water resistant sunscreen if swimming or sweating
- Sun Protection Measures:Spending time in the sun increases your risk of skin cancer and early skin aging. To decrease this risk, regularly use a sunscreen with a Broad Spectrum SPF 15 or higher and other sun protection measures including:
- Limit time in the sun, especially from 10 a.m. - 2 p.m.
- Wear long-sleeved shirts, pants, hats, and sunglasses
- Children under 6 months of age: ask a doctor

SHAKE WELL BEFORE USE

Other information

Protect the product in this container from excessive heat and direct sun.

Inactive ingredients

WATER/EAU (AQUA), DIMETHICONE, C12-15 ALKYL BENZOATE, PHENYL TRIMETHICONE, TALC, PEG-10 DIMETHICONE, DIMETHICONE/VINYL DIMETHICONE CROSSPOLYMER, TRIMETHYLSILOXYSILICATE, GLYCERIN, ISOSTEARYL NEOPENTANOATE, GLYCERYL GLUCOSIDE, BIS-PEG/PPG-14/14 DIMETHICONE, ISODODECANE, PHENOXYETHANOL, SODIUM CHLORIDE, MICA, MAGNESIUM SULFATE, MENTHOXYPROPANEDIOL, SODIUM DEHYDROACETATE, HYDROGEN DIMETHICONE, TRIETHOXYCAPRYLYLSILANE, BENZOIC ACID, C24-28 ALKYL METHICONE, DISTEARDIMONIUM HECTORITE, SILICA, ALUMINUM HYDROXIDE, DEHYDROACETIC ACID, VACCINIUM MYRTILLUS FRUIT EXTRACT, PROPYLENE CARBONATE, ETHYLHEXYLGLYCERIN, LAURETH-4, POTASSIUM SORBATE, SODIUM BENZOATE, LACTIC ACID, PENTAERYTHRITYL TETRA-DI-T-BUTYL HYDROXYHYDROCINNAMATE: +/- MAY CONTAIN: TITANIUM DIOXIDE (CI 77891), IRON OXIDES (CI 77491), IRON OXIDES (CI 77492), IRON OXIDES (CI 77499)

Active ingredients

Zinc Oxide 6.7%

Purpose

Sunscreen

Uses

- Helps prevent sunburn
- If uses directed with others sun protection measures (see Directions) decreases the risk of skin cancer and early skin aging caused by the sun.

Warnings

For external use only.

Do not use

on damaged or broken skin.

When using this product

keep out of eyes. Rinse with water to remove.

Stop use and ask a doctor if

rash occurs.

Keep out of reach of children.

If swallowed, get medical help or contact a Poison Control Center right away.

Directions

- Apply generously 15 minutes before sun exposure
- Reapply at least every 2 hours
- Use a water resistant sunscreen if swimming or sweating
- Sun Protection Measures:Spending time in the sun increases your risk of skin cancer and early skin aging. To decrease this risk, regularly use a sunscreen with a Broad Spectrum SPF 15 or higher and other sun protection measures including:
- Limit time in the sun, especially from 10 a.m. - 2 p.m.
- Wear long-sleeved shirts, pants, hats, and sunglasses
- Children under 6 months of age: ask a doctor

SHAKE WELL BEFORE USE

Other information

Protect the product in this container from excessive heat and direct sun.

Inactive ingredients

WATER/EAU (AQUA), DIMETHICONE, C12-15 ALKYL BENZOATE, PHENYL TRIMETHICONE, TALC, PEG-10 DIMETHICONE, DIMETHICONE/VINYL DIMETHICONE CROSSPOLYMER, TRIMETHYLSILOXYSILICATE, GLYCERIN, ISOSTEARYL NEOPENTANOATE, GLYCERYL GLUCOSIDE, BIS-PEG/PPG-14/14 DIMETHICONE, ISODODECANE, PHENOXYETHANOL, SODIUM CHLORIDE, MICA, MAGNESIUM SULFATE, MENTHOXYPROPANEDIOL, SODIUM DEHYDROACETATE, HYDROGEN DIMETHICONE, TRIETHOXYCAPRYLYLSILANE, BENZOIC ACID, C24-28 ALKYL METHICONE, DISTEARDIMONIUM HECTORITE, SILICA, ALUMINUM HYDROXIDE, DEHYDROACETIC ACID, VACCINIUM MYRTILLUS FRUIT EXTRACT, PROPYLENE CARBONATE, ETHYLHEXYLGLYCERIN, LAURETH-4, POTASSIUM SORBATE, SODIUM BENZOATE, LACTIC ACID, PENTAERYTHRITYL TETRA-DI-T-BUTYL HYDROXYHYDROCINNAMATE: +/- MAY CONTAIN: TITANIUM DIOXIDE (CI 77891), IRON OXIDES (CI 77491), IRON OXIDES (CI 77492), IRON OXIDES (CI 77499)